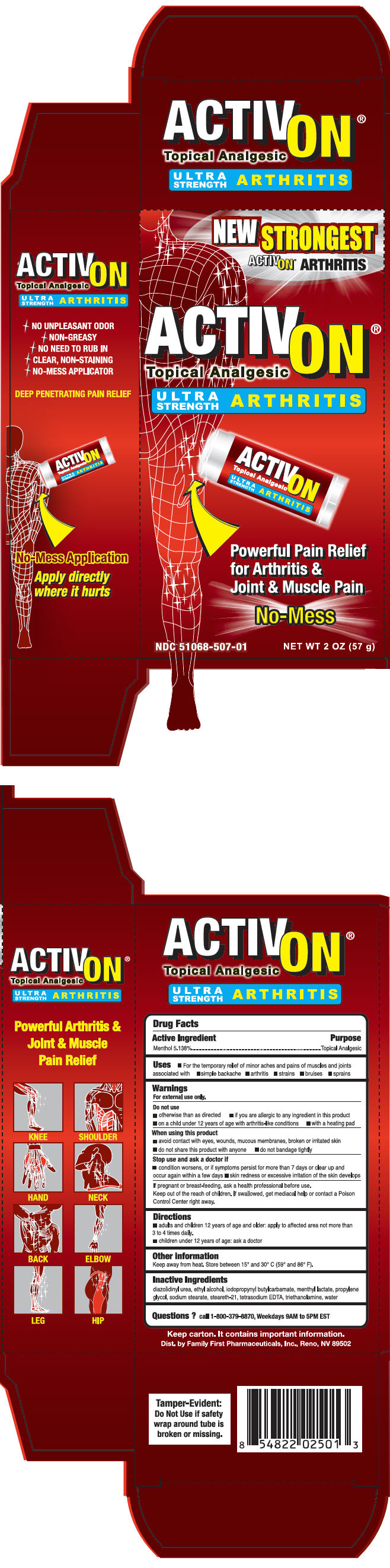 DRUG LABEL: ActivOn Ultra Strength Arthritis
NDC: 51068-507 | Form: STICK
Manufacturer: Family First Pharmaceuticals, Inc.
Category: otc | Type: HUMAN OTC DRUG LABEL
Date: 20170221

ACTIVE INGREDIENTS: Menthol, Unspecified Form 0.05138 g/1 g
INACTIVE INGREDIENTS: diazolidinyl urea; alcohol; iodopropynyl butylcarbamate; menthyl lactate, (-)-; propylene glycol; sodium stearate; steareth-21; Edetate Sodium; trolamine; water

ActivOn® Ultra Strength Arthritis

Drug Facts

Active Ingredient

Menthol 5.138%

Purpose

Topical Analgesic

Uses

- For the temporary relief of minor aches and pains of muscles and joints associated with
  - simple backache
  - arthritis
  - strains
  - bruises
  - sprains

Warnings

For external use only.

Do not use

- otherwise than as directed
- if you are allergic to any ingredient in this product
- on a child under 12 years of age with arthritis-like conditions
- with a heating pad

When using this product

- avoid contact with eyes, wounds, mucous membranes, broken or irritated skin
- do not share this product with anyone
- do not bandage tightly

Stop use and ask a doctor if

- condition worsens, or if symptoms persist for more than 7 days or clear up and occur again within a few days
- skin redness or excessive irritation of the skin develops

PREGNANCY OR BREAST FEEDING

If pregnant or breast-feeding, ask a health professional before use.

KEEP OUT OF REACH OF CHILDREN

Keep out of the reach of children. If swallowed, get mediacal help or contact a Poison Control Center right away.

Directions

- adults and children 12 years of age and older: apply to affected area not more than 3 to 4 times daily.
- children under 12 years of age: ask a doctor

Other information

Keep away from heat. Store between 15° and 30° C (59° and 86° F).

Inactive Ingredients

diazolidinyl urea, ethyl alcohol, iodopropynyl butylcarbamate, menthyl lactate, propylene glycol, sodium stearate, steareth-21, tetrasodium EDTA, triethanolamine, water

Questions ?

call 1-800-379-8870, Weekdays 9AM to 5PM EST

Dist. by Family First Pharmaceuticals, Inc., Reno, NV 89502

PRINCIPAL DISPLAY PANEL - 57 g Canister Carton

NEW STRONGEST

ACTIVON® ARTHRITIS

ACTIVON®
Topical Analgesic

ULTRA
STRENGTH
ARTHRITIS

Powerful Pain Relief
for Arthritis &
Joint & Muscle Pain

No-Mess

NDC 51068-507-01
NET WT 2 OZ (57 g)